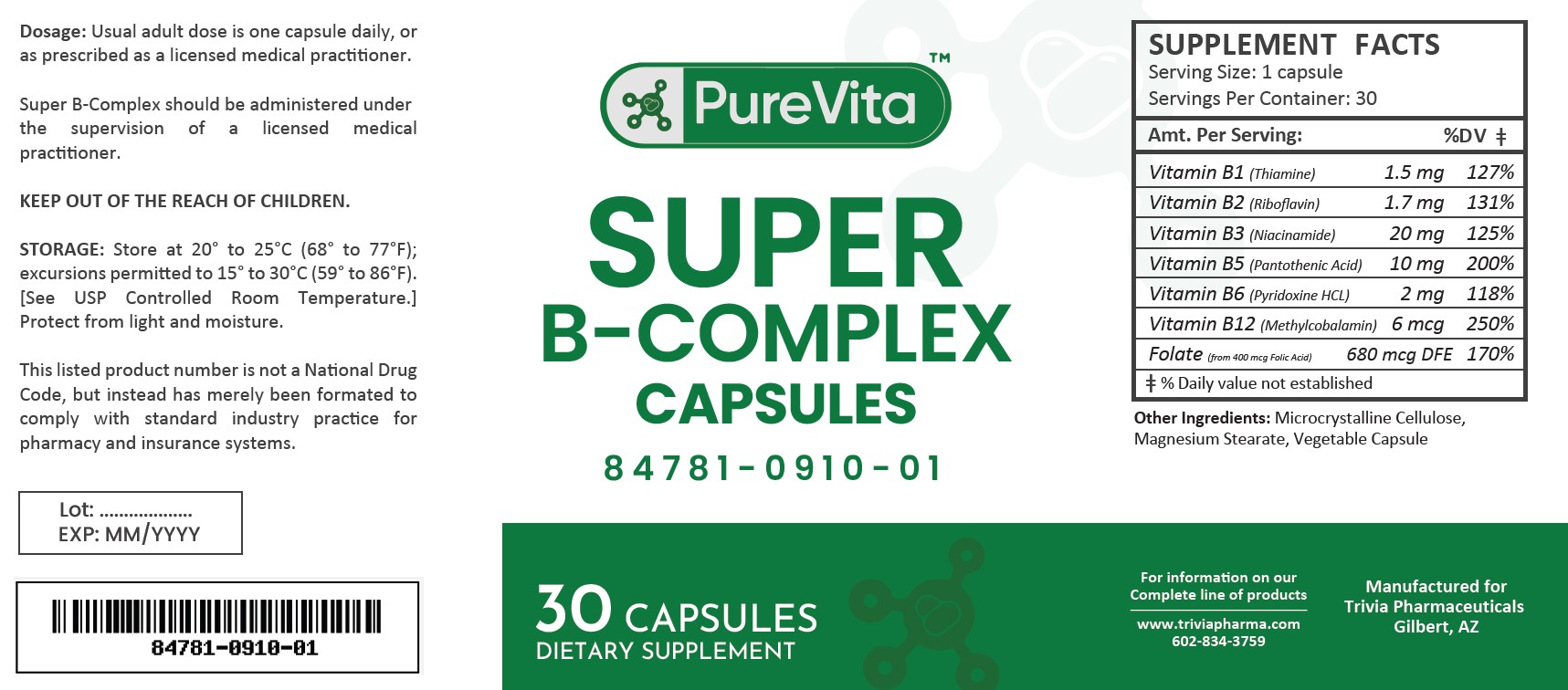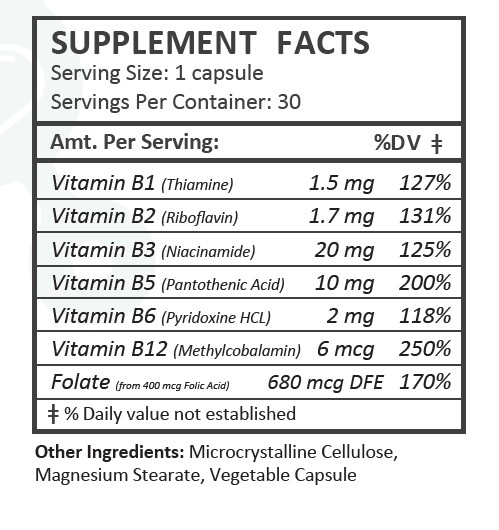 DRUG LABEL: PureVita B-Complex
NDC: 84781-910 | Form: CAPSULE
Manufacturer: Trivia Pharmaceuticals, LLC
Category: other | Type: Dietary Supplement
Date: 20250307

ACTIVE INGREDIENTS: THIAMINE HCL 1.5 mg/1 1; RIBOFLAVIN 1.7 mg/1 1; NIACINAMIDE 20 mg/1 1; PANTOTHENIC ACID 10 mg/1 1; PYRIDOXINE HYDROCHLORIDE 2 mg/1 1; METHYLCOBALAMIN 6 ug/1 1; FOLIC ACID 680 ug/1 1
INACTIVE INGREDIENTS: MICROCRYSTALLINE CELLULOSE; MAGNESIUM STEARATE

PureVita B-Complex Capsules

Health Claim Section:

PureVita Super B-Complex Caps

Description:

PureVita Super B-Complex capsules is an orally administered prescription vitamin to provide significant amounts of B Vitamins and folate to supplement the diet, and to help assure that nutritional deficiencies of these vitamines will not develop.

PureVita Super B-Complex capsules should be administered under the supervision of a licensed medical practitioner.

This listed product is not a National Drug Code, but instead has merely been formatted to comply with standard industry practice for pharmacy and insurance computer systems.

Warnings and Precautions:

This product is contraindicated in patients with a known hypersensitivity to any of the ingredients.

PureVita Super-B Complex capsules should only be used under the direction and supervision of a licensed medical practitioner. Use with caution in patients that may have a medical condition, are pregnant, lactating, trying to conceive, under the age of 18, or taking medications.

Dosage and Administration:

Usual adult dose is 1 capsule by mouth daily once daily, or as prescribed by a licensed medical practitioner.

How Supplied:

PureVita Super B-Complex Capsules is supplied as clear capsules dispensed in plastic bottles of 30 ct.

84781-910-01

Reserved for Professional Recommendation

All prescriptions using this product shall be pursuant to state statutes as applicable. This is not an Orange Book product. This product may be administered only under a physician’s supervision. There are no implied or explicit claims on therapeutic equivalence.

Manufactured for:
Trivia Pharmaceuticals

Gilbert, AZ

Storage:

Store at 20° to 25°C (68° to 77°F); excursions permitted to 15° to 30°C (59° to 86°F). [See USP Controlled Room Temperature.] Protect from light and moisture.